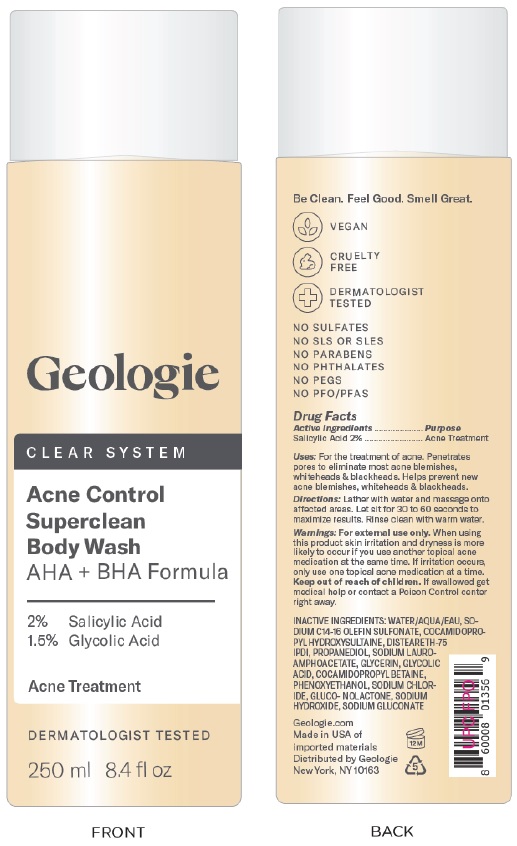 DRUG LABEL: Acne Control Superclean Body Wash
NDC: 54111-170 | Form: GEL
Manufacturer: Bentley Laboratories, LLC
Category: otc | Type: HUMAN OTC DRUG LABEL
Date: 20241227

ACTIVE INGREDIENTS: SALICYLIC ACID 2.0 g/100 mL
INACTIVE INGREDIENTS: WATER; SODIUM C14-16 OLEFIN SULFONATE; COCAMIDOPROPYL HYDROXYSULTAINE; DISTEARETH-75 ISOPHORONE DIISOCYANATE; PROPANEDIOL; SODIUM LAUROAMPHOACETATE; GLYCERIN; GLYCOLIC ACID; COCAMIDOPROPYL BETAINE; PHENOXYETHANOL; SODIUM CHLORIDE; GLUCONOLACTONE; SODIUM HYDROXIDE; SODIUM GLUCONATE

Geologie Acne Control Superclean Body Wash AHA+ BHA Formula

DRUG FACTS

Active Ingredients........... Salicylic Acid 2%

Purpose ............... Acne Treatment

INDICATIONS AND USAGE

Uses: For the treatment of acne. Penetrates pores to eliminate most acne blemishes, whiteheads & blackheads. Helps prevent new acne blemishes, whiteheads & blackheads.

DOSAGE AND ADMINISTRATION

Directions: Lather with water and massage onto affected areas. Let sit for 30 to 60 seconds to maximize results. Rinse clean with warm water.

WARNINGS

Warnings: For external use only. When using this product skin irritation and dryness is more likely to occur if you use another topical acne medication at the same time. If irritation occurs, only use one topical acne medication at a time.

KEEP OUT OF REACH OF CHILDREN

Keep out of the reach of children. If swallowed get medical help or contact a Poison Control center right away.

INACTIVE INGREDIENT

INACTIVE INGREDIENTS: WATER/AQUA/EAU, SODIUM C14-16 OLEFIN SULFONATE, COCAMIDOPROPYL HYDROXYSULTAINE, DISTEARETH-75 IPDI, PROPANEDIOL, SODIUM LAUROAMPHOACETATE, GLYCERIN, GLYCOLIC ACID, COCAMIDOPROPYL BETAINE, PHENOXYETHANOL, SODIUM CHLORIDE, GLUCO-NOLACTONE, SODIUM HYDROXIDE, SODIUM GLUCONATE

Geologie Clear System Package Labeling

Geologie

CLEAR SYSTEM

Acne Control

Superclean

Body Wash

250 mL 8.4 fl oz

Geologie.com

Distributed by Geologie

New York, NY 10163

res